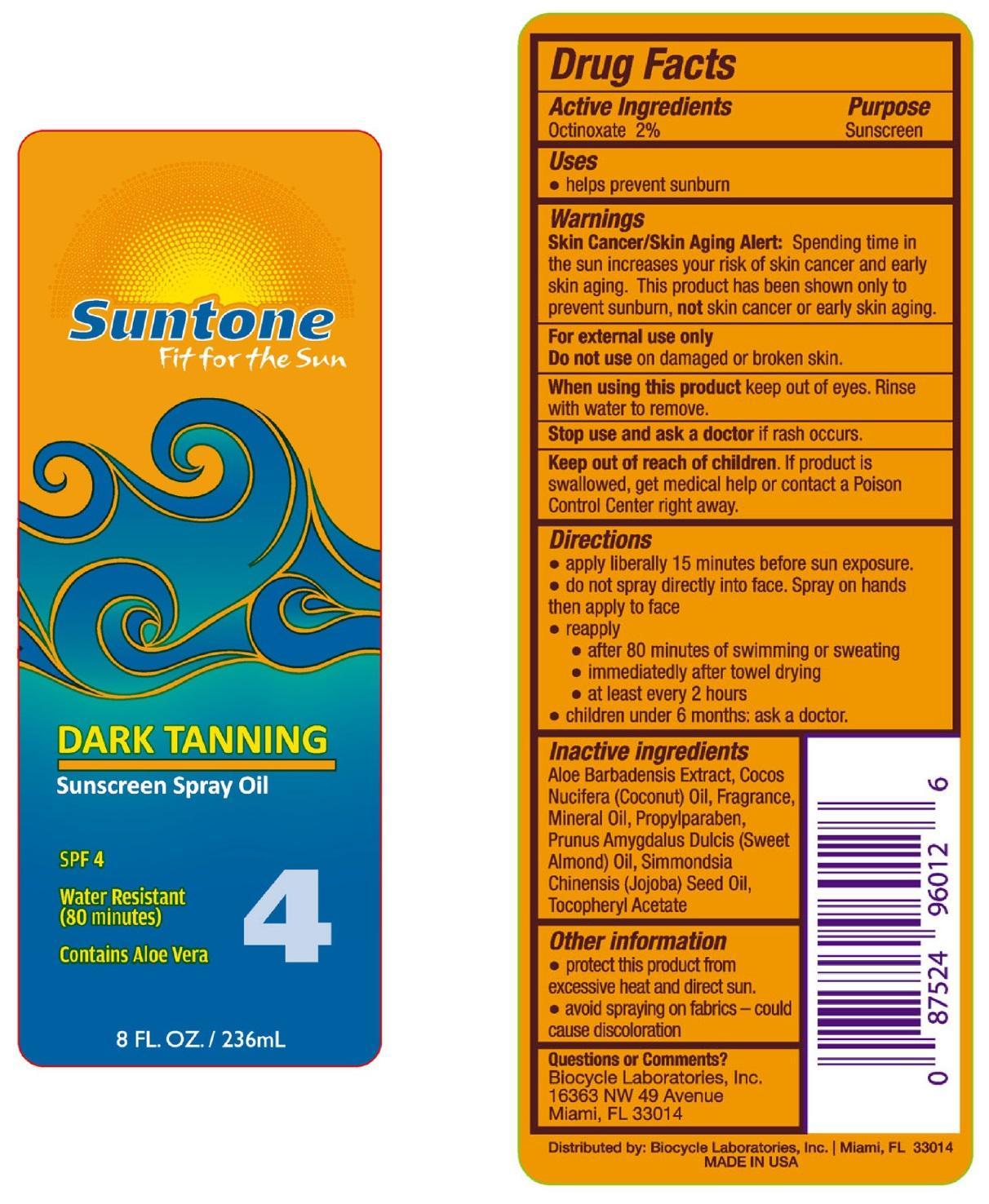 DRUG LABEL: Suntone
NDC: 58443-0098 | Form: SPRAY
Manufacturer: Prime Enterprises, Inc.
Category: otc | Type: HUMAN OTC DRUG LABEL
Date: 20200117

ACTIVE INGREDIENTS: OCTINOXATE 16.7 mg/1 mL
INACTIVE INGREDIENTS: COCONUT OIL; MINERAL OIL; ALOE VERA FLOWER; PROPYLPARABEN; ALMOND OIL; JOJOBA OIL; .ALPHA.-TOCOPHEROL ACETATE

Active ingredients

Octinoxate 2 %

Purpose

Sunscreen

Uses

- helps prevent sunburn

Warnings

Skin Cancer/Skin Aging Alert: Spending time in the sun increases your risk of skin cancer and early skin aging. This product has been shown only to prevent sunburn, not skin cancer or early skin aging.

OTHER SAFETY INFORMATION

For external use only

Do not use on damaged or broken skin.

When using this product keep out of eyes. Rinse with water to remove.

Stop use and ask a doctor if rash occurs.

Keep out of reach of children. If product is swallowed, get medical help or contact a Poison Control Center right away.

Directions

- apply liberally 15 minutes before sun exposure.
- do not spray directly into face. Spray on hands then apply to face
- reapply:
  - after 80 minutes of swimming or sweating
  - immediately after towel drying
  - at least every 2 hour
- children under 6 months: ask a doctor.

Inactive Ingredients

Aloe Barbadensis Extract, Cocos Nucifera (Coconut) Oil, Fragrance (Parfum), Mineral Oil (Paraffinum Liquidum), Propylparaben, Prunus Amygdalus Dulcis (Sweet Almond) Oil, Simmondsia Chinensis (Jojoba) Seed Oil, Tocopheryl Acetate

Other information

- protect this product from excesive heat and direct sun.
- avoid spraying on fabrics - could cause discoloration

Questions or Comments?

Biocycle Laboratories, Inc.

16363 NW 49 Avenue

Miami, FL 33014

PRINCIPAL DISPLAY PANEL - 236 mL Bottle Label

Suntone

Fit for the Sun

DARK TANNING

Sunscreen Spray Oil

SPF 4

Water Resistant

(80 Minutes)

4

Contains Aloe Vera

8 FL. OZ./236mL